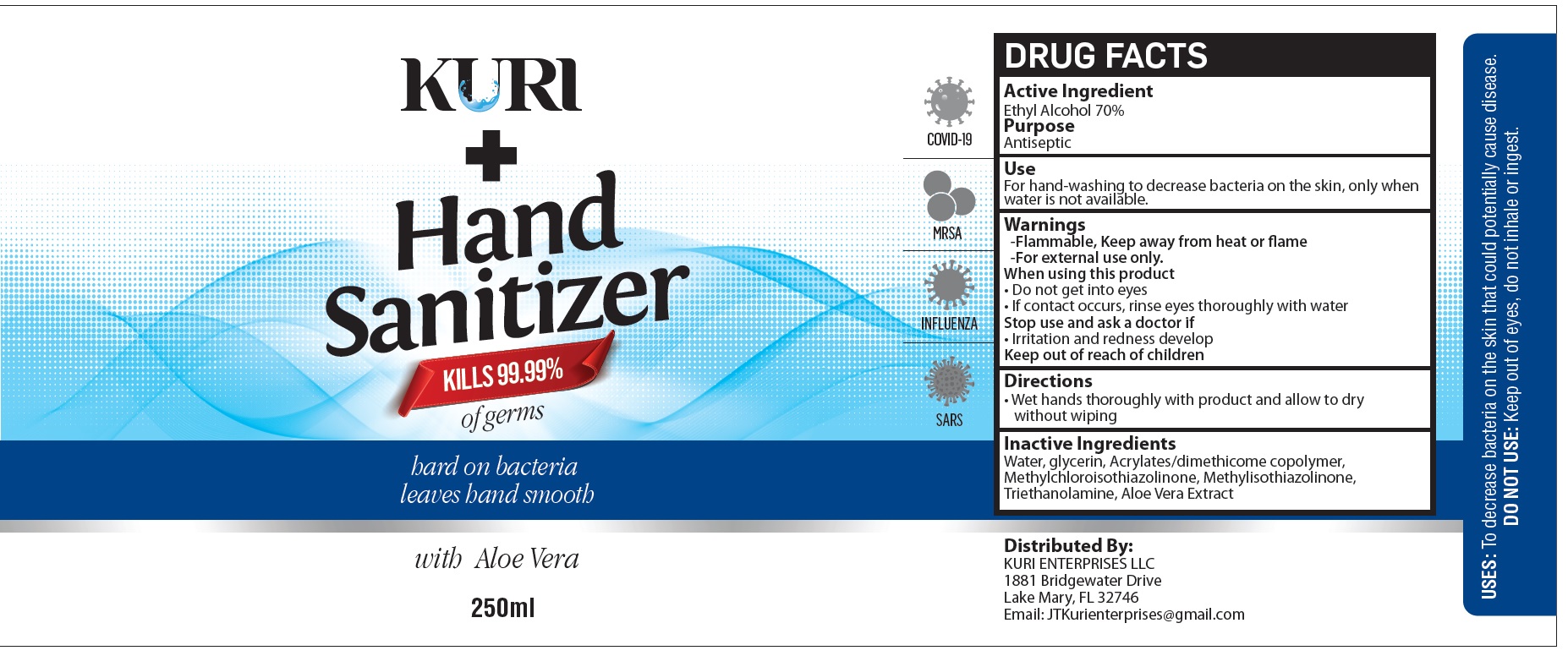 DRUG LABEL: Kuri Hand Sanitizer
NDC: 79560-001 | Form: LIQUID
Manufacturer: Kuri Enterprises
Category: otc | Type: HUMAN OTC DRUG LABEL
Date: 20200714

ACTIVE INGREDIENTS: ALCOHOL 0.7 mL/1 mL
INACTIVE INGREDIENTS: WATER; GLYCERIN; METHYLCHLOROISOTHIAZOLINONE; METHYLISOTHIAZOLINONE; TROLAMINE; ALOE VERA LEAF

Kuri Hand Sanitizer

Active Ingredient

Ethyl Alcohol 70%

Purpose

Antiseptic

Use

For hand-washing to decrease bacteria on the skin, only when water is not available.

Warnings

-Flammable, Keep away from heat or flame

-For external use only.

When using this product

- Do not get into eyes
- If contact occurs, rinse eyes thoroughly with water

Stop use and ask a doctor if

- Irritation and redness develop

Directions

- Wet hands thoroughly with product and allow to dry without wiping

Inactive Ingredients

Water, glycerin, Acrylates/dimethicome copolymer, Methylchloroisothiazolinone, Methylisothiazolinone, Triethanolamine, Aloe Vera Extract